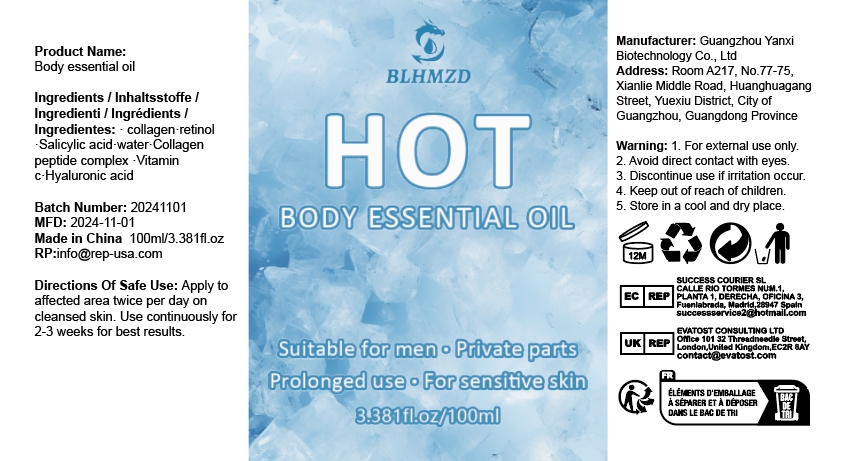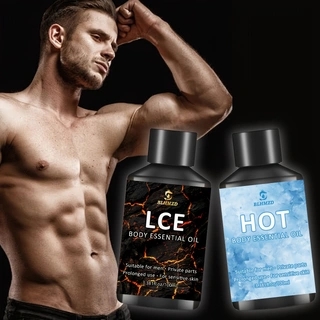 DRUG LABEL: Body essential oil
NDC: 84025-304 | Form: LIQUID
Manufacturer: Guangzhou Yanxi Biotechnology Co., Ltd
Category: otc | Type: HUMAN OTC DRUG LABEL
Date: 20250106

ACTIVE INGREDIENTS: RETINOL 3 mg/100 mL; HYALURONIC ACID 5 mg/100 mL
INACTIVE INGREDIENTS: WATER

DOSAGE AND ADMINISTRATION

Apply to affected area twice per day on cleansed skin.Use continuously for2-3 weeks for best results.

INACTIVE INGREDIENT

Aqua

INDICATIONS AND USAGE

For daily skin care

WARNINGS

Keep out of children

Keep out of children

PURPOSE

Suitable for men private parts